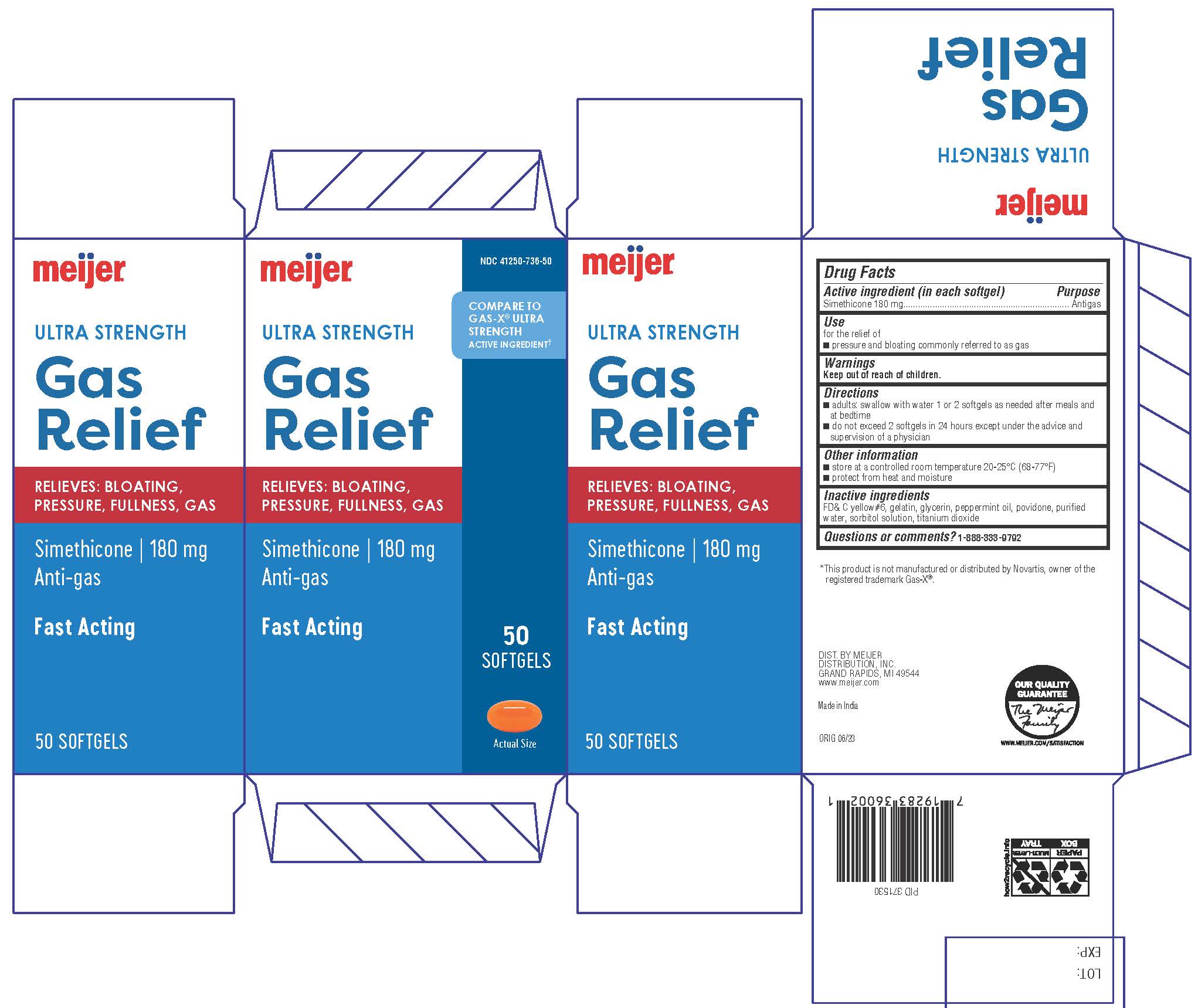 DRUG LABEL: Ultra Strength Gas Relief
NDC: 41250-736 | Form: CAPSULE, LIQUID FILLED
Manufacturer: Meijer Distribution Inc.
Category: otc | Type: HUMAN OTC DRUG LABEL
Date: 20241220

ACTIVE INGREDIENTS: DIMETHICONE 180 mg/1 1
INACTIVE INGREDIENTS: FD&C YELLOW NO. 6; GELATIN; GLYCERIN; PEPPERMINT OIL; POVIDONE K30; WATER; SORBITOL; TITANIUM DIOXIDE

Meijer Ultra Strength Gas Relief

Drug Facts

Active ingredient (in each softgel)

Simethicone 180 mg

Purpose

Antigas

Uses

for the relief of
■ pressure and bloating commonly referred to as gas

Warnings

Keep out of reach of children.

Keep out of reach of children.

Directions

■adults: swallow with water 1 or 2 softgels as needed after meals and
at bedtime
■ do not exceed 2 softgels in 24 hours except under the advice and
supervision of a physician

Other information

■ store at a controlled room temperature 20-25°C (68-77°F)
■ protect from heat and moisture

Inactive ingredients

FD&C yellow #6, gelatin, glycerin, peppermint oil, povidone, purified
water, sorbitol solution, titanium dioxide

Questions or comments? 1-888-333-9792

DISTRIBUTED BY:

MEIJER DISTRIBUTION, INC.

GRAND RAPIDS, MI 49544

PRINCIPAL DISPLAY PANEL

Compare to the active
ingredient in Gas-X®
Ultra Strength Softgels*
Simethicone 180mg

Anti-gas

Fast Relief of:

Bloating

Pressure

Fullness

Gas

Easy to swallow softgels

50 Softgels